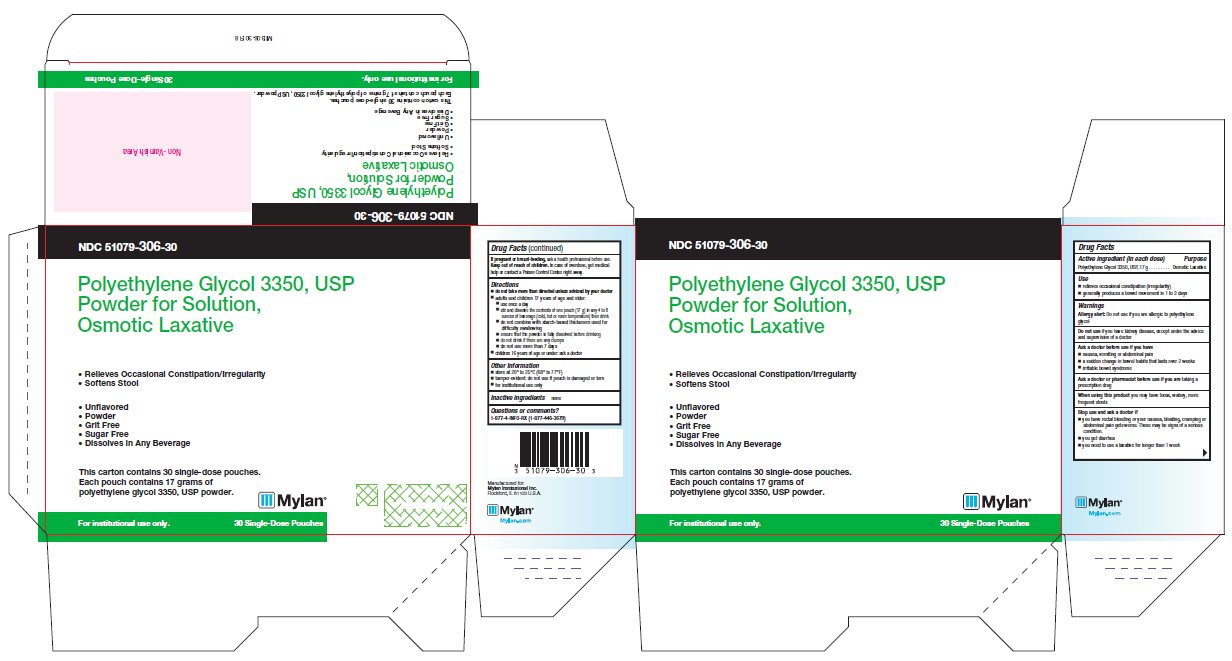 DRUG LABEL: Polyethylene Glycol (3350)
NDC: 51079-306 | Form: POWDER, FOR SOLUTION
Manufacturer: Mylan Institutional Inc.
Category: otc | Type: HUMAN OTC DRUG LABEL
Date: 20240716

ACTIVE INGREDIENTS: POLYETHYLENE GLYCOL 3500 17 g/17 g

Drug Facts

Active ingredient (in each dose)

Polyethylene Glycol 3350, USP, 17 g

Purpose

Osmotic Laxative

Use

- relieves occasional constipation (irregularity)
- generally produces a bowel movement in 1 to 3 days

Warnings

Allergy alert:Do not use if you are allergic to polyethylene glycol

Do not use

if you have kidney disease, except under the advice and supervision of a doctor

Ask a doctor before use if you have

- nausea, vomiting or abdominal pain
- a sudden change in bowel habits that lasts over 2 weeks
- irritable bowel syndrome

Ask a doctor or pharmacist before use if you are

taking a prescription drug

When using this product

you may have loose, watery, more frequent stools

Stop use and ask a doctor if

- you have rectal bleeding or your nausea, bloating, cramping or abdominal pain gets worse. These may be signs of a serious condition.
- you get diarrhea
- you need to use a laxative for longer than 1 week

If pregnant or breast-feeding,

ask a health professional before use.

Keep out of reach of children.

In case of overdose, get medical help or contact a Poison Control Center right away.

Directions

- do not take more than directed unless advised by your doctor
- adults and children 17 years of age and older:
  - use once a day
  - stir and dissolve the contents of one pouch (17 g) in any 4 to 8 ounces of beverage (cold, hot or room temperature) then drink
  - do not combine with starch-based thickeners used for difficulty swallowing
  - ensure that the powder is fully dissolved before drinking
  - do no drink if there are any clumps
  - do not use more than 7 days
- children 16 years of age or under: ask a doctor

Other Information

- store at 20° to 25°C (68° to 77°F)
- tamper-evident: do not use if pouch is damaged or torn
- for institutional use only

Inactive ingredients

none

Questions or comments?

1-877-4-INFO-RX (1-877-446-3679)

Manufactured for:
Mylan Institutional Inc.
Rockford, IL 61103 U.S.A.

MII306-30:R8

Principal Display Panel

NDC 51079-306-30

Polyethylene Glycol 3350, USP
Powder for Solution,
Osmotic Laxative

- Relieves Occasional Constipation/Irregularity
- Softens Stool

- Unflavored
- Powder
- Grit Free
- Sugar Free
- Dissolves in Any Beverage

This carton contains 30 single-dose pouches.
Each pouch contains 17 grams of
polyethylene glycol 3350, USP powder.

For institutional use only. 30 Single-Dose Pouches